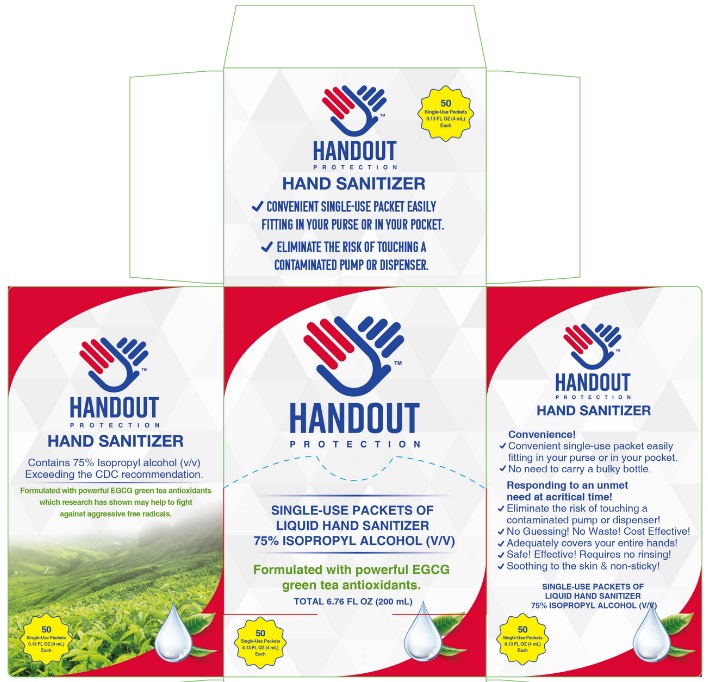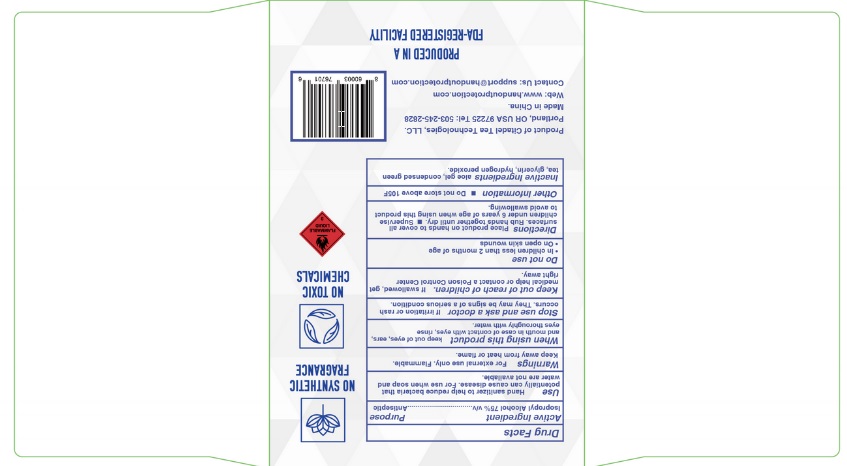 DRUG LABEL: HANDOUT protection hand sanitizer
NDC: 73928-012 | Form: LIQUID
Manufacturer: KINGKEY MBC LIFE TECHNOLOGY GROUP CO., LTD
Category: otc | Type: HUMAN OTC DRUG LABEL
Date: 20251007

ACTIVE INGREDIENTS: ISOPROPYL ALCOHOL 75 mL/100 mL
INACTIVE INGREDIENTS: ALOE VERA LEAF; GREEN TEA LEAF; GLYCERIN; HYDROGEN PEROXIDE

Active Ingredient

lsopropyl Alcohol 75% v/v

Purpose

Antiseptic

Use

Hand Sanitizer to help reduce bacteria that potentially can cause disease. For use when soap and water are not available.

Warnings

For external use only. Flammable. Keep away from heat or flame

WHEN USING

When using this productkeep out of eyes, ears, and mouth. In case of contact with eyes, rinse eyes thoroughly with water.

Stop use and ask a doctor ifirritation or rash occurs. These may be signs of a serious condition.

Keep out of reach of children.If swallowed, get medical help or contact a Poison Control Center right away.

Do not use
• In children less than 2 months of age
• On open skin wounds

Directions

- Place enough product on hands to cover all surfaces. Rub hands together until dry.
- Supervise children under 6 years of age when using this product to avoid swallowing.

Other information

Do not store above 105F

Inactive ingredients

aloe gel, condensed green tea, glycerin, Hydrogen peroxide